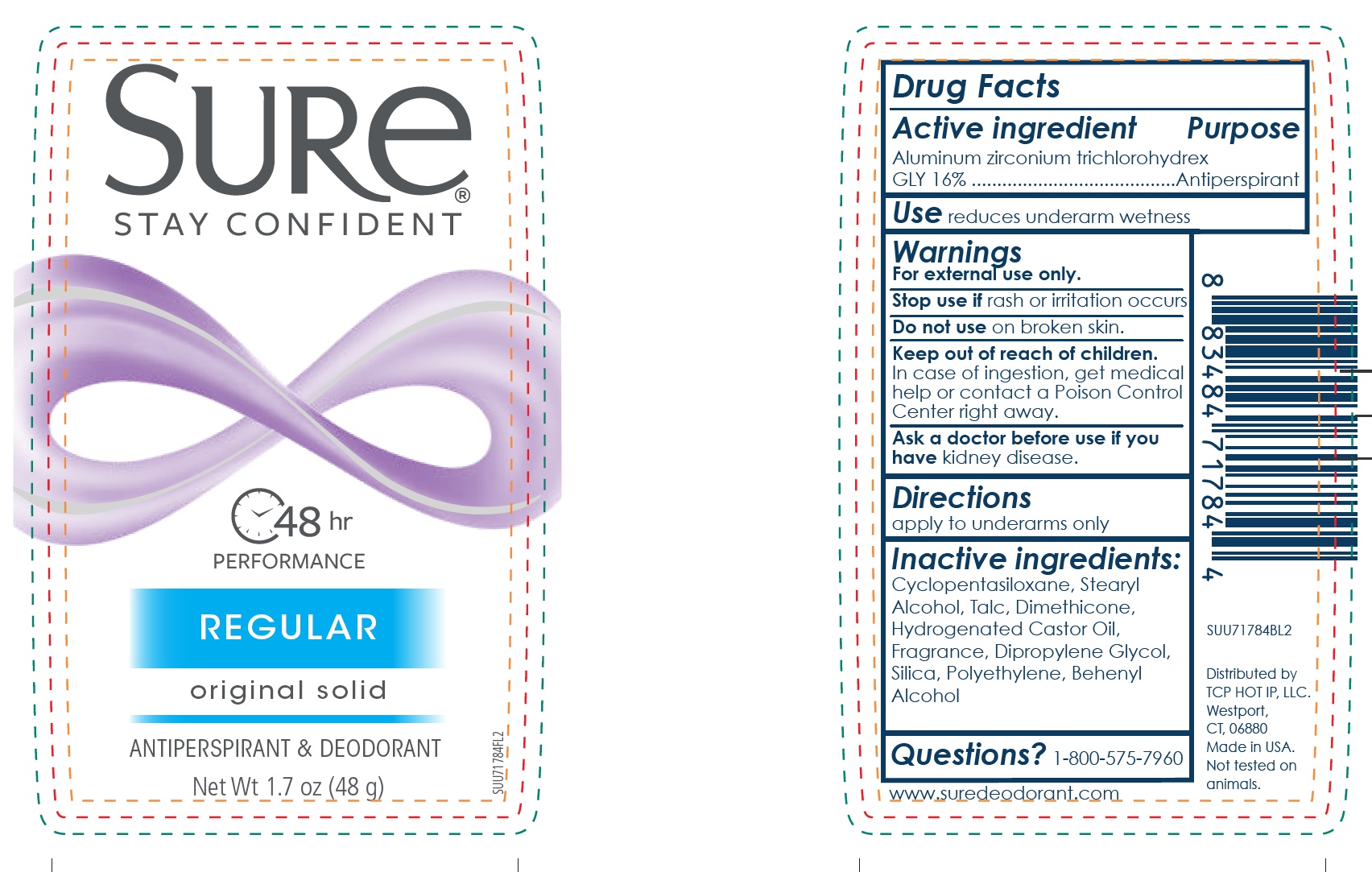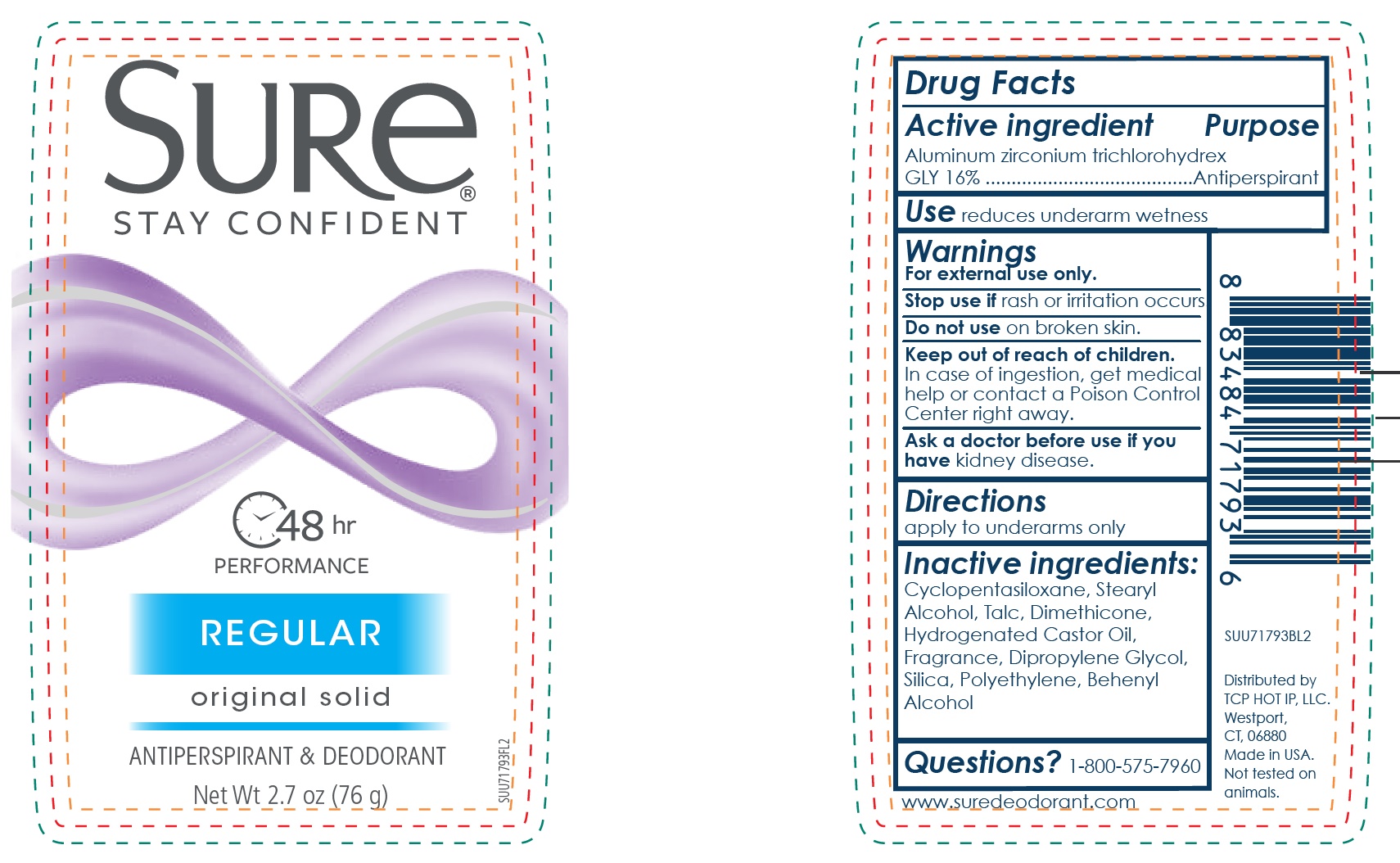 DRUG LABEL: Sure Regular Original Solid
NDC: 81277-004 | Form: STICK
Manufacturer: Sodalis USA LLC
Category: otc | Type: HUMAN OTC DRUG LABEL
Date: 20241108

ACTIVE INGREDIENTS: ALUMINUM ZIRCONIUM TRICHLOROHYDREX GLY 19 g/100 g
INACTIVE INGREDIENTS: CYCLOMETHICONE 5; STEARYL ALCOHOL; TALC; DIMETHICONE; HYDROGENATED CASTOR OIL; DIPROPYLENE GLYCOL; SILICON DIOXIDE; HIGH DENSITY POLYETHYLENE; DOCOSANOL

Sure Regular Original Solid

Active ingredient

Aluminum Zirconium trichlorohydrex GLY 16%

Purpose

Antiperspirant

Use

reduces underarm wetness

Warnings

For external use only.

Stop use if

rash or irritation occurs.

Do not use

on broken skin.

Keep out of reach of children.

In case of ingestion, get medical help or contact a Poison Control Center right away.

Ask a doctor before use if you have

kidney disease.

Directions

apply to underarms only.

Inactive ingredients:

Cyclopentasiloxane, Stearyl Alcohol, Talc, Dimethicone, Hydrogenated Castor Oil, Fragrance, Dipropylene Glycol, Silica, Polyethylene, Behenyl Alcohol

Questions?

1-800-575-7960